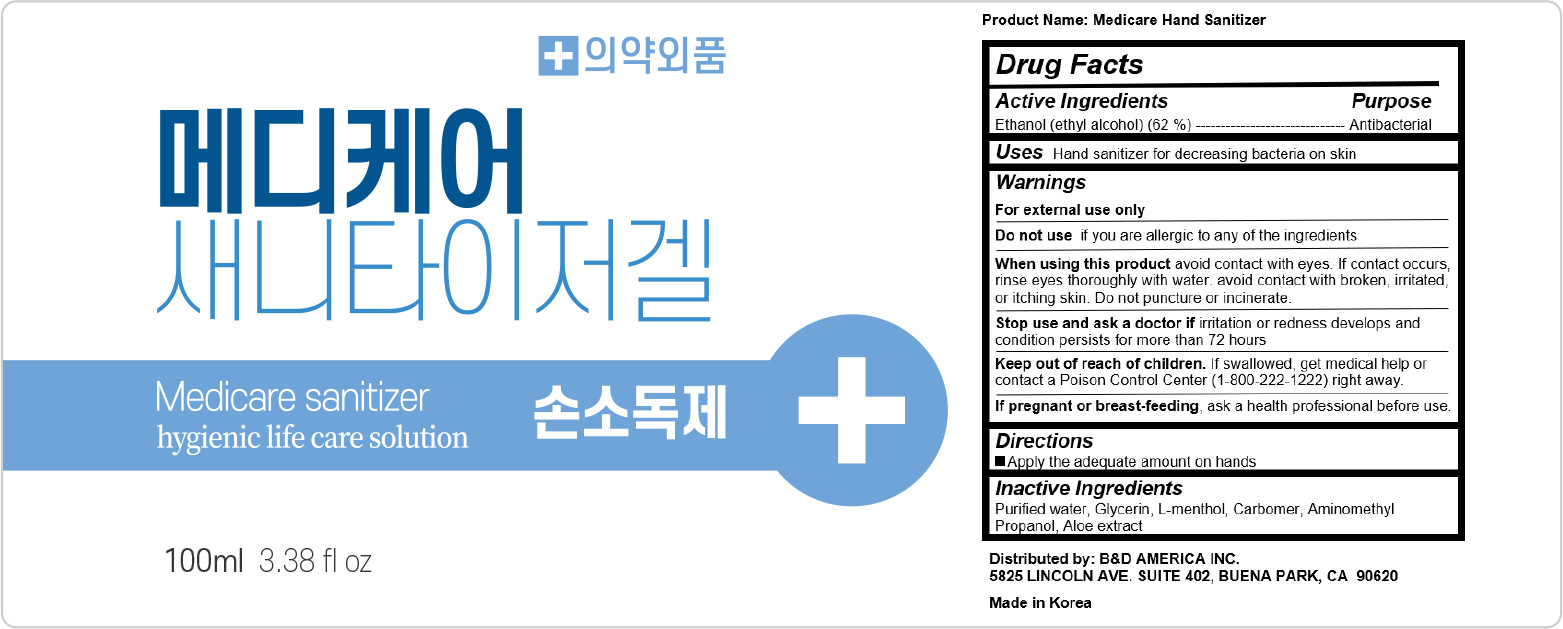 DRUG LABEL: Medicare Hand Sanitizer (100ml)
NDC: 73786-100 | Form: GEL
Manufacturer: B&D LIFE HEALTH CO., LTD.
Category: otc | Type: HUMAN OTC DRUG LABEL
Date: 20220106

ACTIVE INGREDIENTS: ALCOHOL 62 g/100 mL
INACTIVE INGREDIENTS: GLYCERIN; LEVOMENTHOL; AMINOMETHYLPROPANOL; ALOE; WATER

Medicare Hand Sanitizer (100ml)

Active ingedient

Ethanol (ethyl alcohol) (62%)

Purpose

Antibacterial

Uses

Hand sanitizer for decreasing bacteria on skin

Warnings

For external use only

Do not use if you are allergic to any of the ingredients

When using this product avoid contact with eyes. If contact occurs, rinse eyes thoroughly with water. avoid contact with broken, irritated, or itching skin. Do not puncture or incinerate.

Stop use and ask a doctor if irritation or redness develops and condition persists for more than 72 hours.

If pregnant or breast-feeding, ask a health professional before use

Keep out of reach of children

If swallowed, get medical help or contact a Poison Control Center (1-800-222-1222) right away.

Directions

Apply the adequate amount on hands

Inactive ingredients

Purified water, Glycerin, L-menthol, Carbomer, Aminomethyl Propanol, Aloe extract